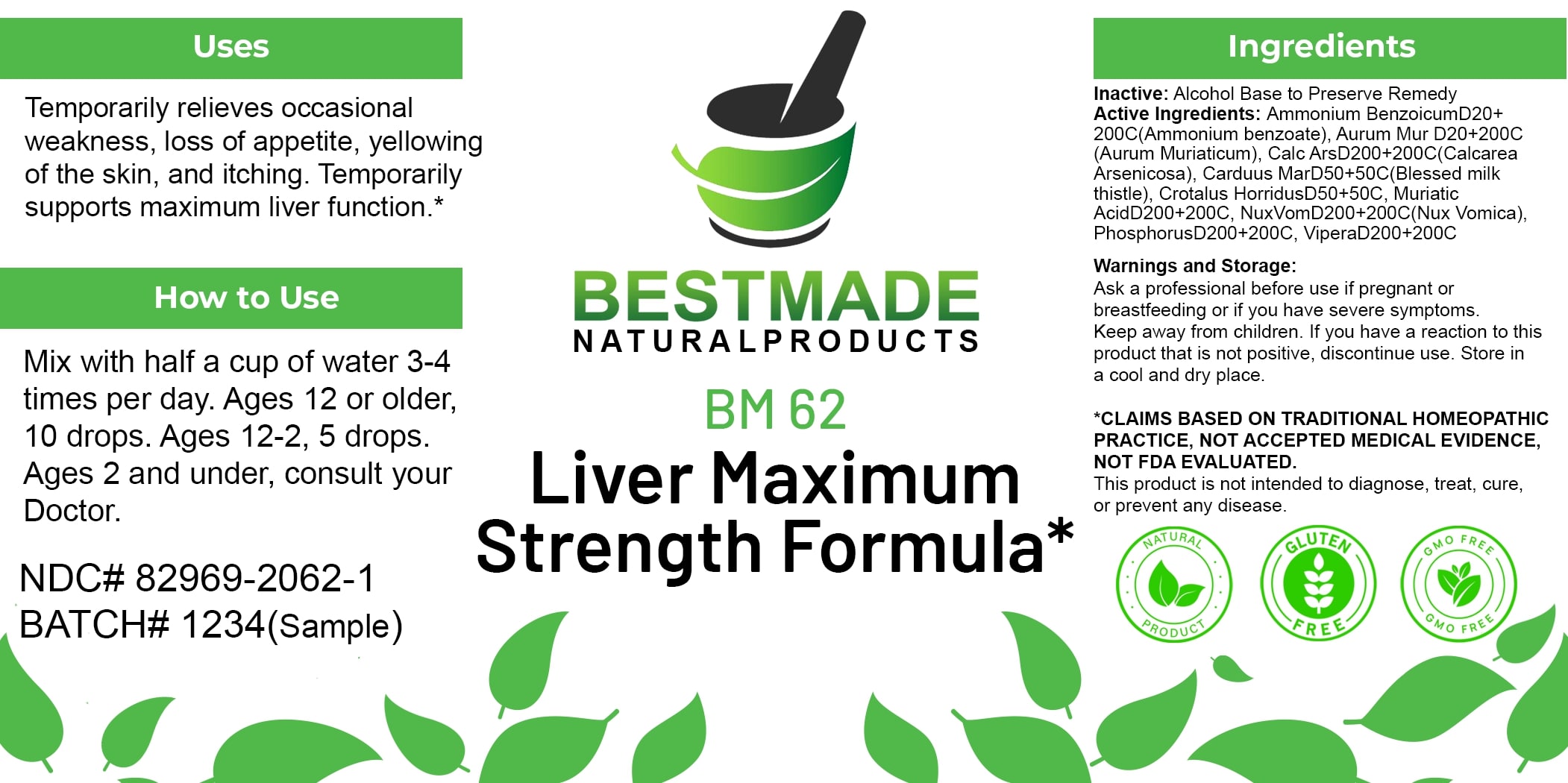 DRUG LABEL: Bestmade Natural Products BM62
NDC: 82969-2062 | Form: LIQUID
Manufacturer: Bestmade Natural Products
Category: homeopathic | Type: HUMAN OTC DRUG LABEL
Date: 20250130

ACTIVE INGREDIENTS: VIPERA BERUS VENOM 200 [hp_C]/200 [hp_C]; MILK THISTLE 200 [hp_C]/200 [hp_C]; AMMONIUM BENZOATE 200 [hp_C]/200 [hp_C]; PHOSPHORUS 200 [hp_C]/200 [hp_C]; CROTALUS HORRIDUS HORRIDUS VENOM 200 [hp_C]/200 [hp_C]; GOLD TRICHLORIDE 200 [hp_C]/200 [hp_C]; HYDROCHLORIC ACID 200 [hp_C]/200 [hp_C]; CALCIUM ARSENATE 200 [hp_C]/200 [hp_C]; STRYCHNOS NUX-VOMICA SEED 200 [hp_C]/200 [hp_C]
INACTIVE INGREDIENTS: ALCOHOL 200 [hp_C]/200 [hp_C]

BM62

DOSAGE AND ADMINISTRATION

How to Use

Mix with half a cup of water 3-4 times per day. Ages 12 or older, 10 drops. Ages 12-2, 5 drops. Ages 2 and under, consult your Doctor.

INACTIVE INGREDIENT

Ingredients

Inactive: Alcohol Base to Preserve Remedy

ACTIVE INGREDIENT

Active Ingredients: Ammonium Benzoicum D20+200C (Ammonium benzoate), Aurum Mur D20+200C (Aurum Muriaticum), Calc Ars D200+200C (Calcarea Arsenicosa), Carduus Mar D50+50C (Blessed milk thistle), Crotalus Horridus D50+50C, Muriatic Acid D200+200C, Nux Vom D200+200C (Nux Vomica), Phosphorus D200+200C, Vipera D200+200C

Uses

Temporarily relieves occasional weakness, loss of appetite, yellowing of the skin, and itching. Temporarily supports maximum liver function.*

*CLAIMS BASED ON TRADITIONAL HOMEOPATHIC PRACTICE, NOT ACCEPTED MEDICAL EVIDENCE. NOT FDA EVALUATED.

This product is not intended to diagnose, treat, cure, or prevent any disease.

Uses

Temporarily relieves occasional weakness, loss of appetite, yellowing of the skin, and itching. Temporarily supports maximum liver function.*

*CLAIMS BASED ON TRADITIONAL HOMEOPATHIC PRACTICE, NOT ACCEPTED MEDICAL EVIDENCE. NOT FDA EVALUATED.

This product is not intended to diagnose, treat, cure, or prevent any disease.

KEEP OUT OF REACH OF CHILDREN

Warnings and Storage:

Ask a professional before use if pregnant or breastfeeding or if you have severe symptoms. Keep away from children. If you have a reaction to this product that is not positive, discontinue use. Store in a cool and dry place.

Warnings and Storage:

Ask a professional before use if pregnant or breastfeeding or if you have severe symptoms. Keep away from children. If you have a reaction to this product that is not positive, discontinue use. Store in a cool and dry place.

*CLAIMS BASED ON TRADITIONAL HOMEOPATHIC PRACTICE, NOT ACCEPTED MEDICAL EVIDENCE. NOT FDA EVALUATED.

This product is not intended to diagnose, treat, cure, or prevent any disease.

Entire package label